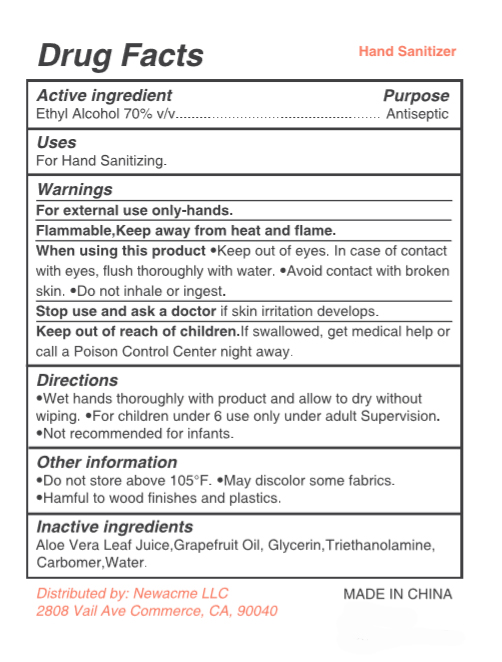 DRUG LABEL: Grape Fruit  Hand Sanitizer
NDC: 77753-005 | Form: GEL
Manufacturer: SHANDISHI Biological Technology Co., Ltd.
Category: otc | Type: HUMAN OTC DRUG LABEL
Date: 20200715

ACTIVE INGREDIENTS: ALCOHOL 70 mL/100 mL
INACTIVE INGREDIENTS: WATER; ALOE VERA LEAF; CARBOMER HOMOPOLYMER, UNSPECIFIED TYPE; VITIS VINIFERA FRUIT OIL; GLYCERIN; TROLAMINE

77753-005 Grape Fruit Hand Sanitizer 70% Alcohol

Active ingredient

Ethyl Alcohol 70% v/v

Purpose

Antiseptic

Uses

For Hand Sanitizing

Warnings

Warnings: For external use only-hands.
Flammable: Keep away from heat and flame.
When using this product Keep out of eyes. In case of
contact with eyes, flush thoroughly with water.●Avoid contact with
broken skin.●Do not inhale or ingest.
Stop use and ask a doctor
if skin irritation develops.

Keep out of reach of children.

If swallowed, get medical help or call a Poison Control Center right away.

Directions

Wet hands thoroughly with product and allow to
dry without wiping●For children under 6 use only under adult
Supervision.●Not recommended for infants.

Other information

Do not store above 105°F
May discolor some fabrics

Hamful to wood finishes and plastics.

Inactive ingredients

Aloe Vera Leaf Juice,Grapefruit Oil, Glycerin,Triethanolamine,Carbomer,Water.